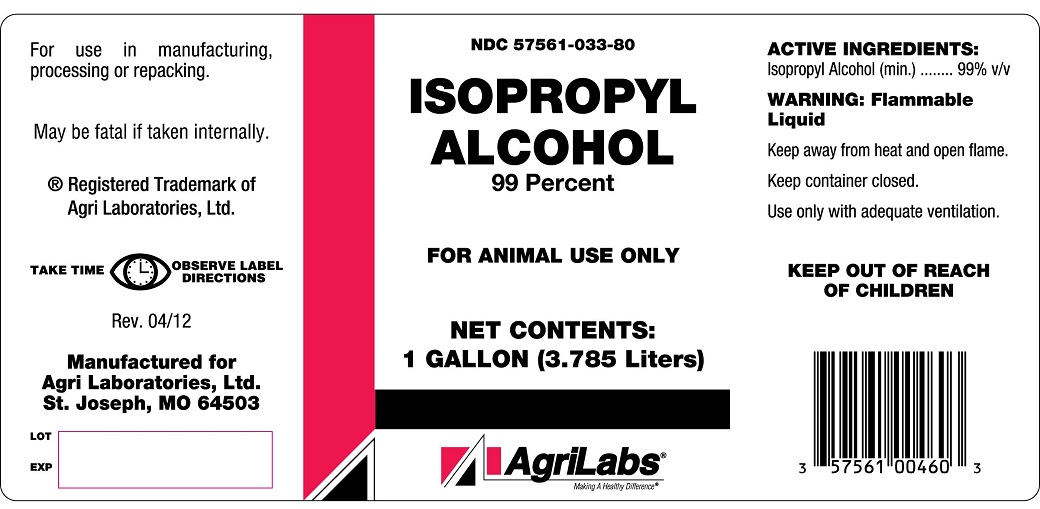 DRUG LABEL: ISOPROPYL ALCOHOL
NDC: 57561-033 | Form: LIQUID
Manufacturer: Agri Laboratories, Inc.
Category: animal | Type: OTC ANIMAL DRUG LABEL
Date: 20141005

ACTIVE INGREDIENTS: ISOPROPYL ALCOHOL 99 L/100 L

Isopropyl Alcohol 99 Percent

DESCRIPTION

FOR ANIMAL USE ONLY

For use in manufacturing, processing or repacking.

May be fatal if taken internally.

TAKE TIME OBSERVE LABEL DIRECTIONS

ACTIVE INGREDIENTS

Isopropyl Alcohol (min.) ...... 99% v/v

WARNING

Flammable Liquid

Keep away from heat and open flame.

Use only with adequate ventilation.

KEEP OUT OF REACH OF CHILDREN